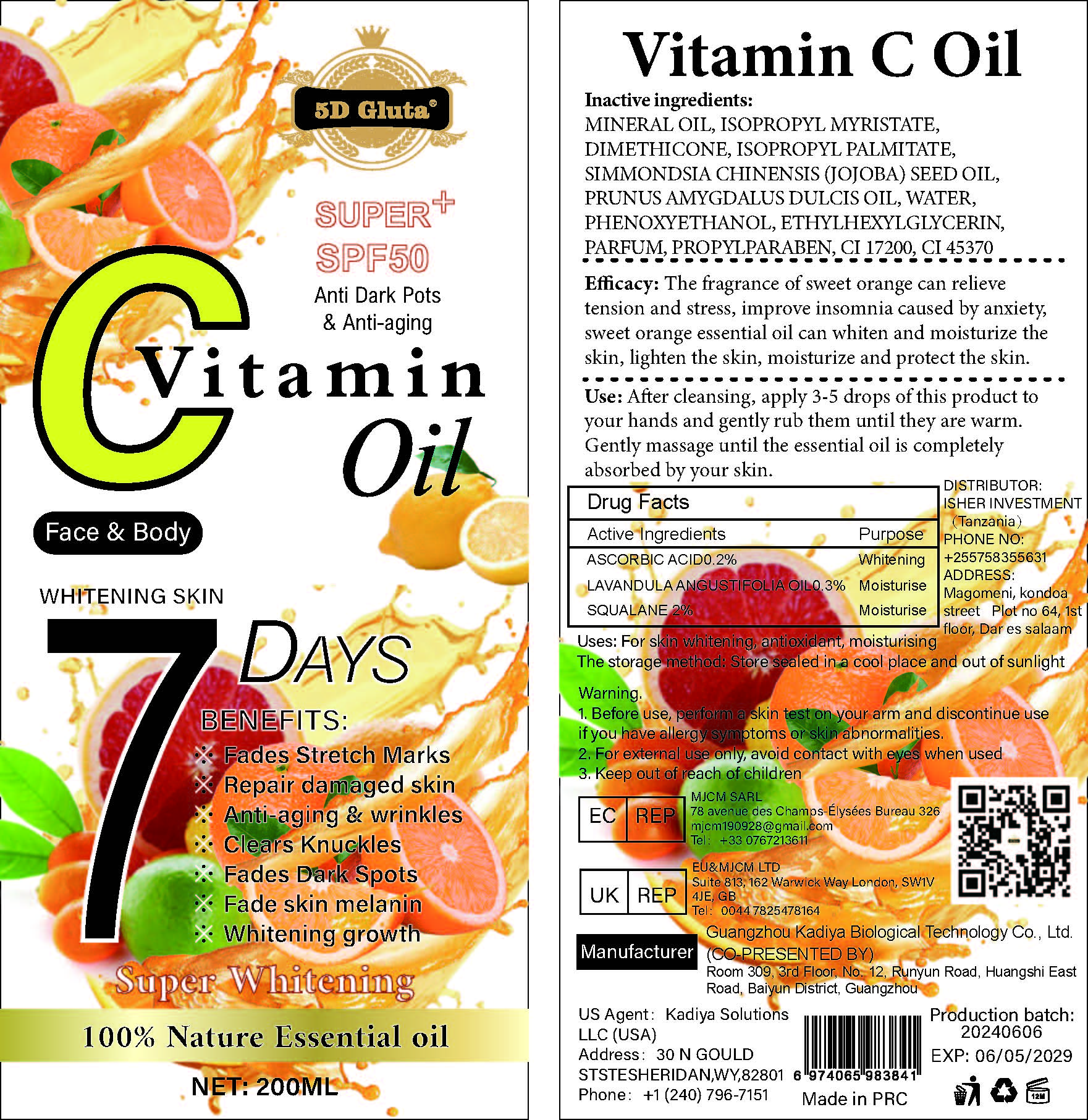 DRUG LABEL: Vitamin C Oil
NDC: 84423-055 | Form: OIL
Manufacturer: Guangzhou Kadiya Biotechnology Co., Ltd.
Category: otc | Type: HUMAN OTC DRUG LABEL
Date: 20241217

ACTIVE INGREDIENTS: ASCORBIC ACID 0.4 g/200 mL; SQUALANE 4 g/200 mL; LAVANDULA ANGUSTIFOLIA (LAVENDER) OIL 0.6 g/200 mL
INACTIVE INGREDIENTS: PROPYLPARABEN; SIMMONDSIA CHINENSIS (JOJOBA) SEED OIL; ISOPROPYL MYRISTATE; MINERAL OIL; CI 17200; PHENOXYETHANOL; ETHYLHEXYLGLYCERIN; CI 45370; ISOPROPYL PALMITATE; WATER; PRUNUS AMYGDALUS DULCIS (SWEET ALMOND) OIL; DIMETHICONE 1000

PURPOSE

For skin whitening, antioxidant, moisturising

INACTIVE INGREDIENT

MINERAL OIL，ISOPROPYL MYRISTATE，DIMETHICONE，ISOPROPYL PALMITATE，SIMMONDSIA CHINENSIS (JOJOBA) SEED OIL， PRUNUS AMYGDALUS DULCIS OIL，WATER，PHENOXYETHANOL，ETHYLHEXYLGLYCERIN，PARFUM，PROPYLPARABEN，CI 17200，CI 45370

WARNINGS

1.Before use, perform a skin test on your arm and discontinue use if you have allergy symptoms or skin abnormalities.
2、For external use only, avoid contact with eyes when used
3、Keep out of reach of children

INDICATIONS AND USAGE

Efficacy: The fragrance of sweet orange can relieve tension and stress, improve insomnia caused by anxiety, sweet orange essential oil can whiten and moisturize the skin, lighten the skin, moisturize and protect the skin.

DOSAGE AND ADMINISTRATION

Use: After cleansing, apply 3-5 drops of this product to your hands and gently rub them until they are warm. Gently massage until the essential oil is completely absorbed by your skin

KEEP OUT OF REACH OF CHILDREN SECTION

Active Ingredients
ASCORBIC ACID0.2%
LAVANDULA ANGUSTIFOLIA OIL0.3%
SQUALANE 2%

PACKAGE LABEL

Active Ingredients
ASCORBIC ACID0.2%
LAVANDULA ANGUSTIFOLIA OIL0.3%
SQUALANE 2%

Uses：
For skin whitening, antioxidant, moisturising
The storage method：
Store sealed in a cool place and out of sunlight

Warning.
1.Before use, perform a skin test on your arm and discontinue use if you have allergy symptoms or skin abnormalities.
2、For external use only, avoid contact with eyes when used
3、Keep out of reach of children

Inactive ingredients：
MINERAL OIL，ISOPROPYL MYRISTATE，DIMETHICONE，ISOPROPYL PALMITATE，SIMMONDSIA CHINENSIS (JOJOBA) SEED OIL， PRUNUS AMYGDALUS DULCIS OIL，WATER，PHENOXYETHANOL，ETHYLHEXYLGLYCERIN，PARFUM，PROPYLPARABEN，CI 17200，CI 45370